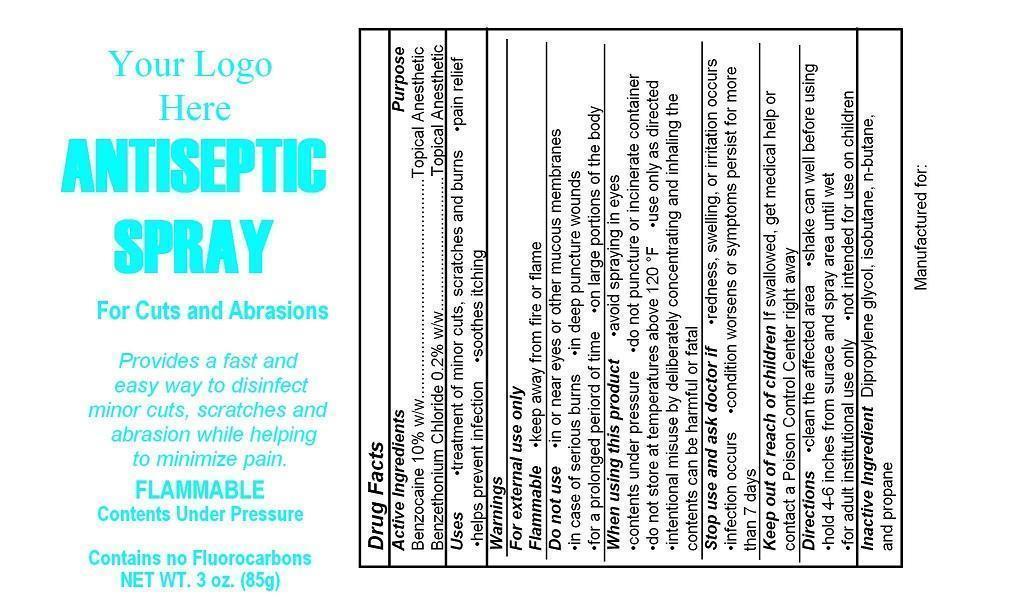 DRUG LABEL: Your Logo Here Antiseptic First Aid
NDC: 52982-100 | Form: AEROSOL, SPRAY
Manufacturer: Dixon Investments, Inc.
Category: otc | Type: HUMAN OTC DRUG LABEL
Date: 20250128

ACTIVE INGREDIENTS: BENZOCAINE 8500 mg/85 g; BENZETHONIUM CHLORIDE 170 mg/85 g
INACTIVE INGREDIENTS: DIPROPYLENE GLYCOL; ISOBUTANE; BUTANE; PROPANE

YOUR LOGO HERE ANTISEPTIC SPRAY

Active Ingredients

Benzocaine 10% w/w
Benzethonium Chloride 0.2% w/w

Purpose

Topical Anesthetic
Topical Antiseptic

Uses

treatment of minor cuts, scratches and burns
pain relief
helps prevent infection
soothes itching

Warnings

For External Use Only

Flammable

keep away from fire or flame

Do not use

in or near eyes or other mucous membranes
in case of serious burns
in deep puncture wounds
for a prolonged period of time
on large portions of the body

When using this product

avoid spraying in the eyes
contents under pressure
do not puncture or incinerate container
do not store at temperatures above 120°F
use only as directed
intentional misuse by deliberately concentrating and inhaling the contents can be harmful or fatal

Stop use and ask doctor if

redness, swelling, or irritation occurs
infection occurs
condition worsens or symptoms persist for more than 7 days

Keep out of reach of children

If swallowed, get medical help or contact a Poison Control Center right away

Directions

clean the affected area
shake can well before using
hold 4-6 inches from surface and spray area until wet
for adult institutional use only
not intended for use on children

Inactive Ingredient

Dipropylene glycol, isobutane, n-butane, and propane